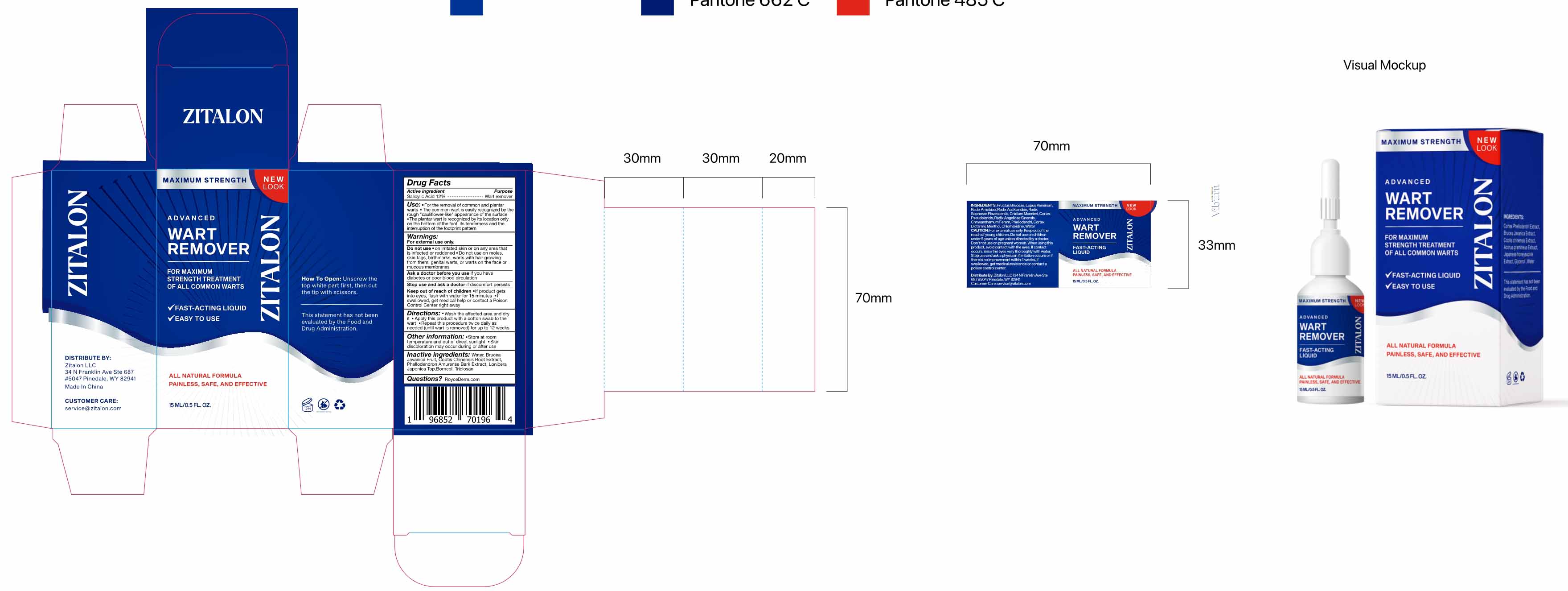 DRUG LABEL: Wart Remover
NDC: 81799-004 | Form: LIQUID
Manufacturer: Ehy Holdings LLC
Category: otc | Type: HUMAN OTC DRUG LABEL
Date: 20221025

ACTIVE INGREDIENTS: SALICYLIC ACID 12 mg/100 mL
INACTIVE INGREDIENTS: COPTIS CHINENSIS ROOT; WATER; PHELLODENDRON AMURENSE BARK; BRUCEA JAVANICA FRUIT; BORNEOL; TRICLOSAN; LONICERA JAPONICA TOP

81799-004
Wart Remover

Active Ingredient(s)

Salicylic Acid 12%

Purpose

Wart remover

Use

for the removal of common and plantar warts
the common war is easy ily recognized by the rough macauli flowerlike " appearance of the surface
the plantar wart is recognized by its location only on the bottom ofthe foot . its tenderness and the interru option of the foot pró nt pattern

Warnings

For externall use

Do not use

on irritated skin or on any area that is infected or reddened
Do not use on moles skin tags , birthmarks , warts with hair growing from them , genital warts , or warts on the face or mucous membranes

Ask a doctor before you use
if you have diabetes or poor blood circulation
Stop use and ask a doctor
if discomfort persists
Keep out of reach of children
If product gets into eyes , flush with water for 15 minutes
IF swallowed , get medical help or contact a Poison Control Center right away

Stop use and ask a doctor
if discomfort persists

Keep out of reach of children
If product gets into eyes , flush with water for 15 minutes
IF swallowed , get medical help or contact a Poison Control Center right away

Directions

Wash the affected area and dry it
Apply this product with a cotton swab to the wart
Repeat this procedure twice daily as needed (until wart is removed) for up to 12 weeks

Other information

Store at room temperature and out of direct sunlight
skin discoloration may occur during or affter use

Inactive ingredients

Water

BRUCEA JAVANICA FRUIT

Coptis Chinensis Root Extract

Phellodendron Amurense Bark Extract

LONICERA JAPONICA TOP

Triclosan

Borneol

Package Label - Principal Display Panel

81799-004-01